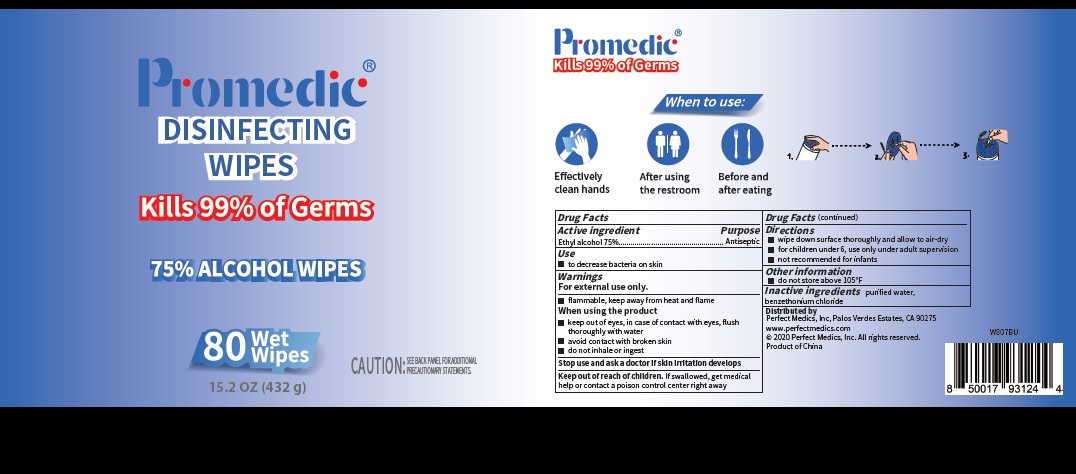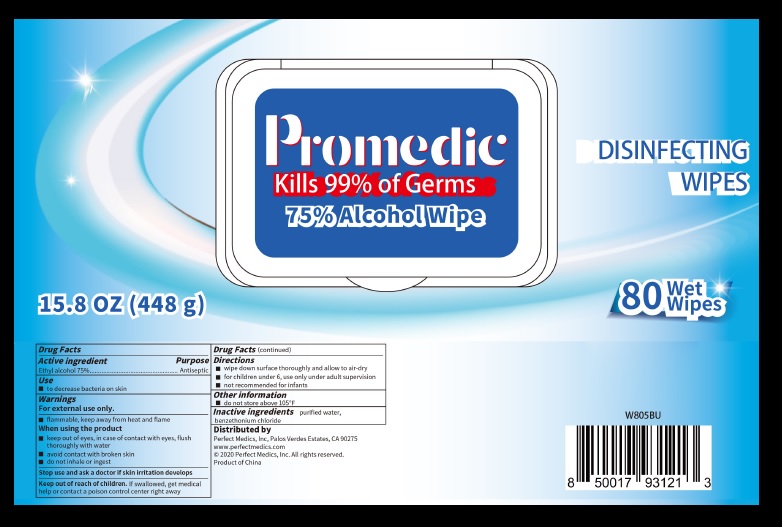 DRUG LABEL: Promedic
NDC: 79134-002 | Form: CLOTH
Manufacturer: Perfect Medics, Inc
Category: otc | Type: HUMAN OTC DRUG LABEL
Date: 20200618

ACTIVE INGREDIENTS: ALCOHOL 75 g/100 g
INACTIVE INGREDIENTS: WATER; BENZETHONIUM CHLORIDE

Promedic DISINFECTING WIPES

Active Ingredients

Ethyl Alcohol 75%

Purpose

Antiseptic

Warnings

For external use only - hands

Flammable, keep away from heat and flame.

When using the product

- keep out of eyes, in case of contact with eyes, flush thoroughly with water.
- avoid contact with broken skin.
- do not inhale or ingest.

Stop use and ask a doctor if skin irritation develops

Uses

- to decrease bacteria on the skin that could cause disease.

Directions

- Wipe down surface thoroughly and allow to air-dry.
- For children under 6, use only under adult supervision.
- Not recommended for infants.

Keep Out of Reach of Children.

- If swallowed, get medical help or contact a poison control center right away.

Other Information

- do not store above 105F

Inactive Ingredients

Purified water, Benzethonium chloride.